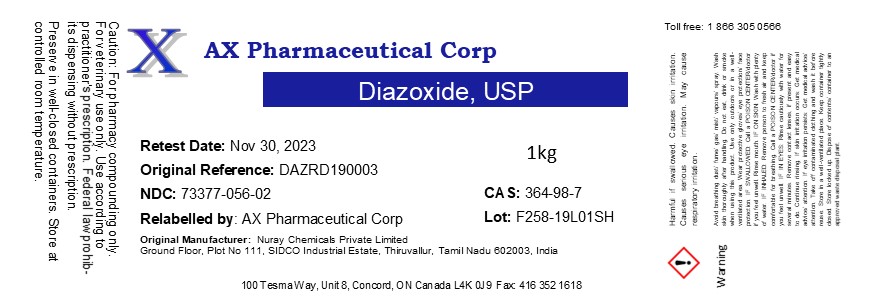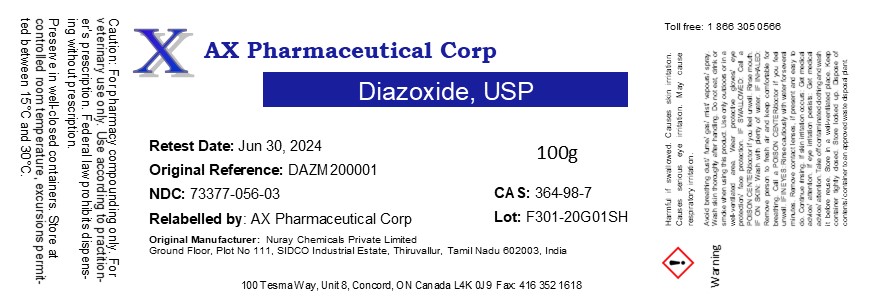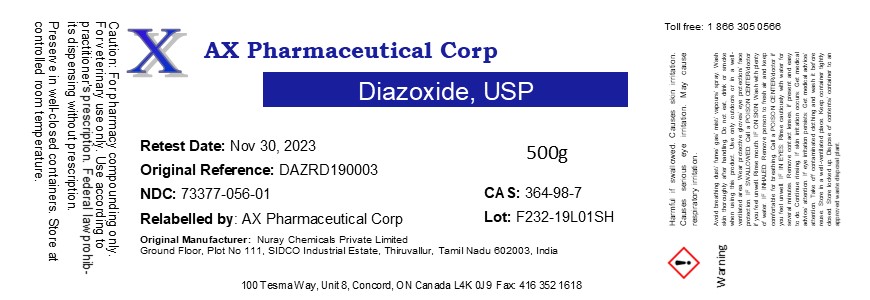 DRUG LABEL: Diazoxide
NDC: 73377-056 | Form: POWDER
Manufacturer: AX Pharmaceutical Corp
Category: other | Type: BULK INGREDIENT
Date: 20200818

ACTIVE INGREDIENTS: DIAZOXIDE 1 g/1 g

Diazoxide